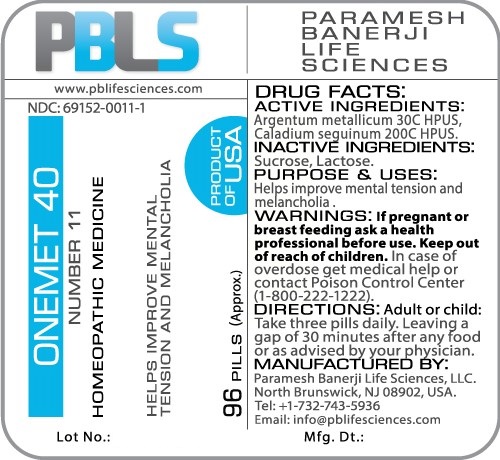 DRUG LABEL: Onemet 40 (Number 11)
NDC: 69152-0011 | Form: PELLET
Manufacturer: Paramesh Banerji Life Sciences LLC
Category: homeopathic | Type: HUMAN OTC DRUG LABEL
Date: 20161110

ACTIVE INGREDIENTS: SILVER 30 [hp_C]/1 1; DIEFFENBACHIA SEGUINE 200 [hp_C]/1 1
INACTIVE INGREDIENTS: SUCROSE; LACTOSE

DRUG FACTS: Active Ingredients

Argentum metallicum 30C HPUS, Caladium seguinum 200C HPUS

Inactive Ingredients

Sucrose, Lactose

Purpose

Helps improve mental tension and melancholia

Uses

Helps improve mental tension and melancholia

Warnings

If pregnant or breast feeding ask a health professional before use.

Keep out of reach of children. In case of overdose, get medical help or contact a Poison Control Center (1-800-222-1222) right away.

Direction

Adult or child: Take three pills daily. Leaving a gap of 30 minutes after any food or as advised by your physician.

Manufactured by

Paramesh Banerji Life Sciences, LLC.

North Brunswick, NJ 08902, USA.

Tel: +1-732-743-5936

Email: info@pblifesciences.com

Principal Display Panel

NDC: 69152-0011-1

Onemet 40

Number 11

Homeopathic Medicine

Helps improve mental tension and melancholia

96 Pills (Approx.)

Product of USA